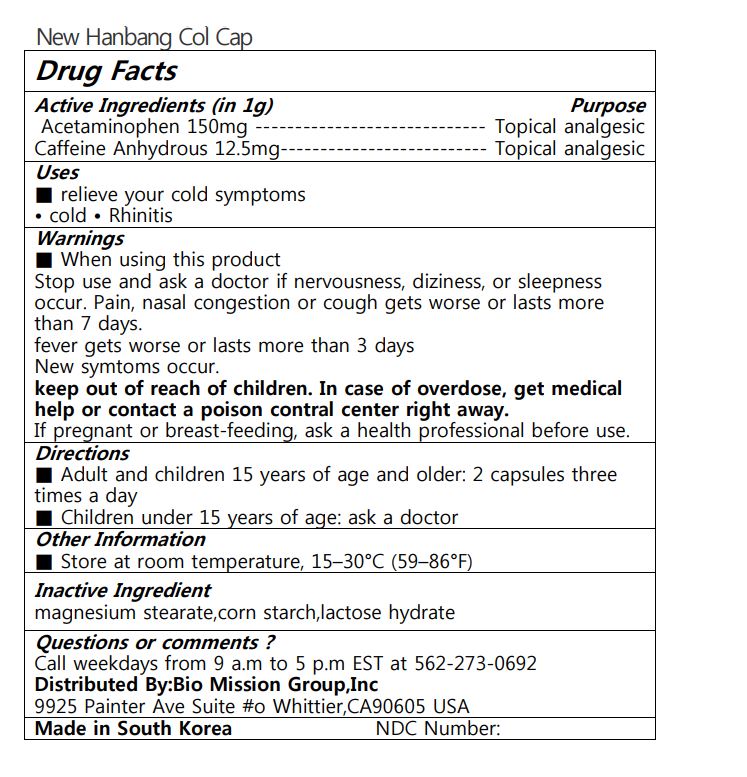 DRUG LABEL: New Hanbang Col Cap
NDC: 72988-0032 | Form: TABLET
Manufacturer: Lydia Co., Ltd.
Category: otc | Type: HUMAN OTC DRUG LABEL
Date: 20230710

ACTIVE INGREDIENTS: ACETAMINOPHEN 150 mg/1 1; CAFFEINE 12.5 mg/1 1
INACTIVE INGREDIENTS: MAGNESIUM STEARATE

ACTIVE INGREDIENT

Acetaminophen, Caffeine Anhydrous,

PURPOSE

■ relieve your cold symptoms • cold • Rhinitis

Keep out of reach of children

INDICATIONS AND USAGE

■ Adult and children 15 years of age and older: 2 capsules three times a day ■ Children under 15 years of age: ask a doctor

■ When using this product Stop use and ask a doctor if nervousness, diziness, or sleepness occur. Pain, nasal congestion or cough gets worse or lasts more than 7 days. fever gets worse or lasts more than 3 days New symtoms occur. keep out of reach of children. In case of overdose, get medical help or contact a poison contral center right away. If pregnant or breast-feeding, ask a health professional before use.

INACTIVE INGREDIENT

magnesium stearate, corn, starch, etc

DOSAGE AND ADMINISTRATION

for oral use